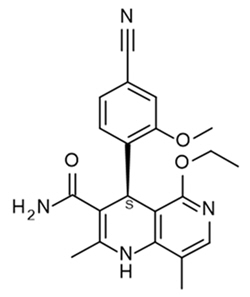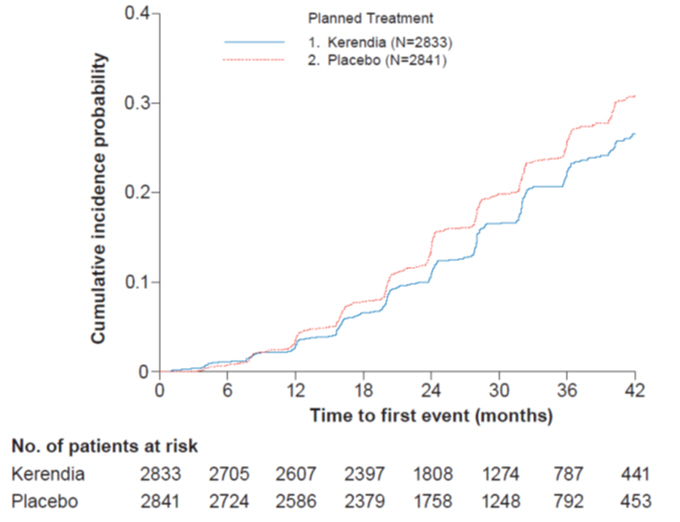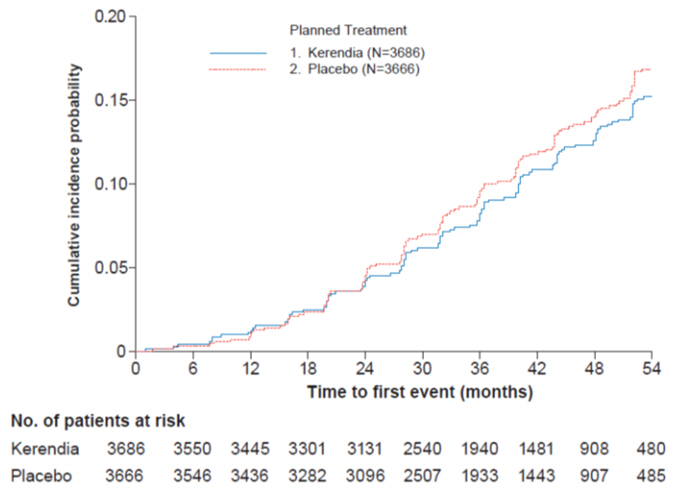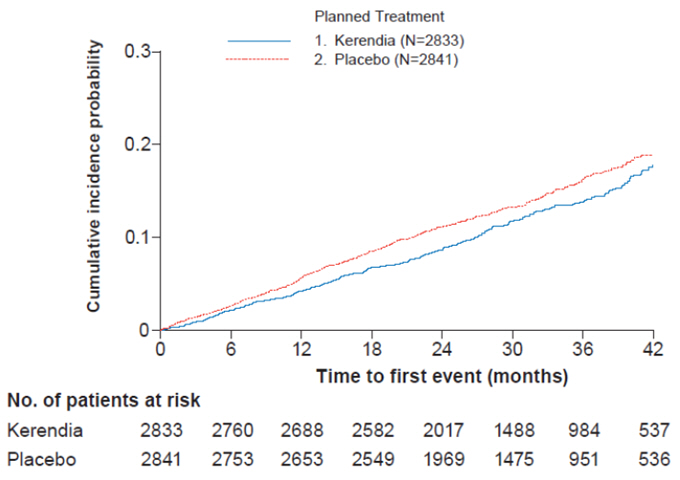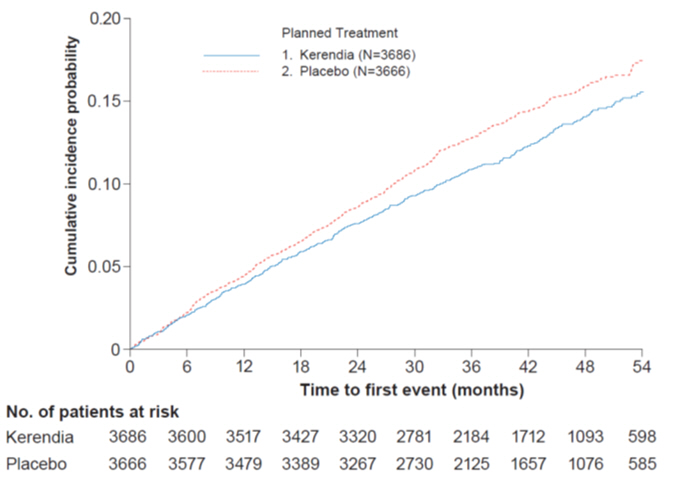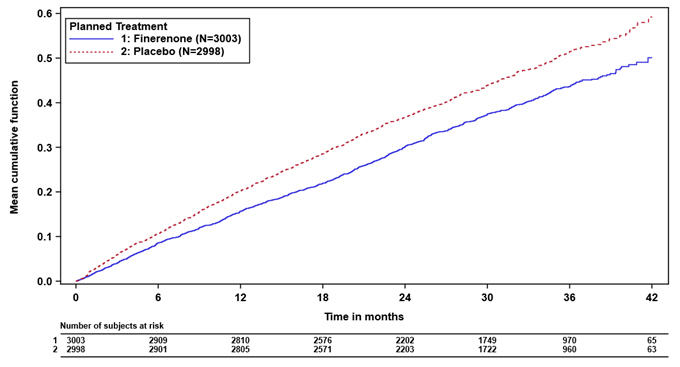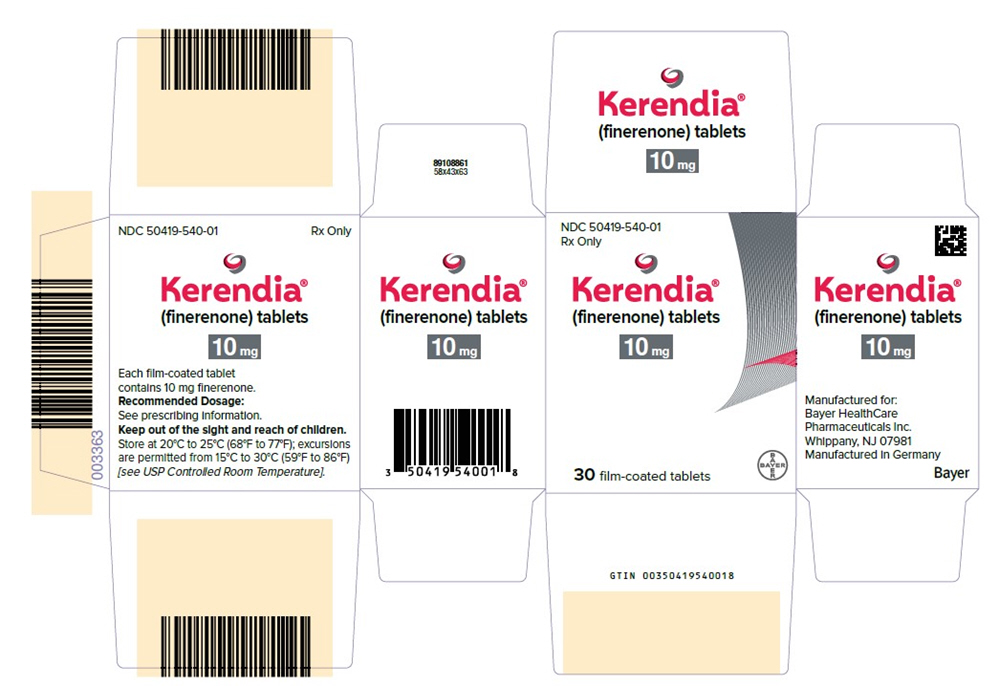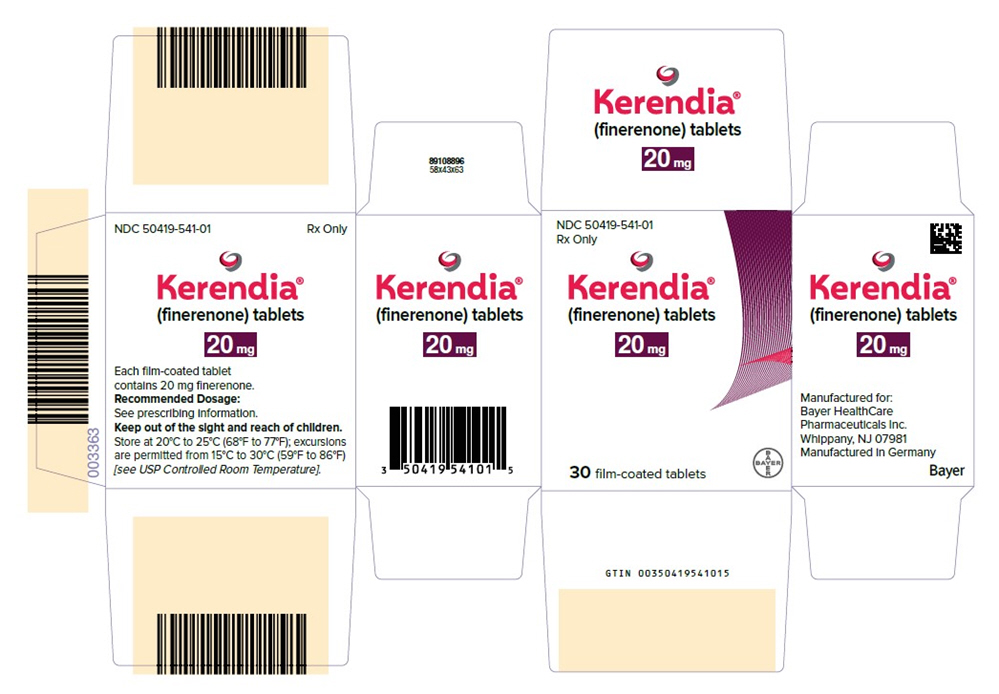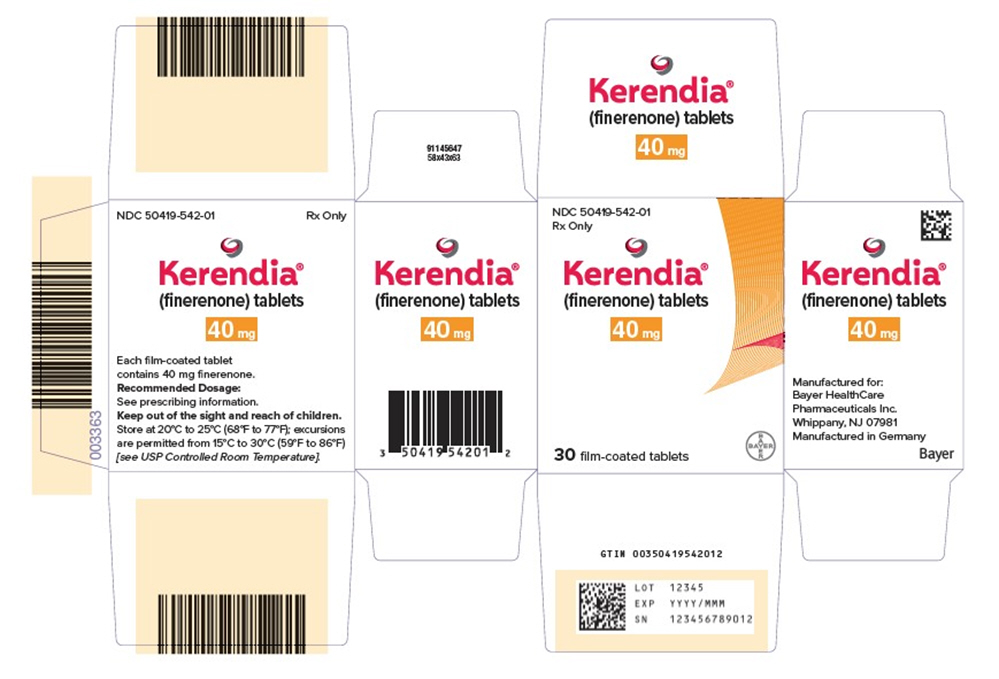 DRUG LABEL: Kerendia
NDC: 50419-540 | Form: TABLET, FILM COATED
Manufacturer: Bayer HealthCare Pharmaceuticals Inc.
Category: prescription | Type: HUMAN PRESCRIPTION DRUG LABEL
Date: 20250828

ACTIVE INGREDIENTS: FINERENONE 10 mg/1 1
INACTIVE INGREDIENTS: LACTOSE MONOHYDRATE; MICROCRYSTALLINE CELLULOSE; CROSCARMELLOSE SODIUM; HYPROMELLOSE, UNSPECIFIED; MAGNESIUM STEARATE; SODIUM LAURYL SULFATE

HIGHLIGHTS OF PRESCRIBING INFORMATION

These highlights do not include all the information needed to use KERENDIA safely and effectively. See full prescribing information for KERENDIA.
KERENDIA (finerenone) tablets, for oral use
Initial U.S. Approval: 2021

RECENT MAJOR CHANGES

Indications and Usage (1) | 7/2025
Dosage and Administration (2.3) | 7/2025
Contraindications (4) | 7/2025
Warnings and Precautions (5.2) | 7/2025

1 INDICATIONS AND USAGE

Kerendia is a non-steroidal mineralocorticoid receptor antagonist (nsMRA) indicated to reduce the risk of:

- sustained estimated glomerular filtration rate (eGFR) decline, end stage kidney disease, cardiovascular death, non-fatal myocardial infarction, and hospitalization for heart failure in adult patients with chronic kidney disease (CKD) associated with type 2 diabetes (T2DM). (1)
- cardiovascular death, hospitalization for heart failure, and urgent heart failure visits in adult patients with heart failure with left ventricular ejection fraction (LVEF) ≥ 40% (1)

2 DOSAGE AND ADMINISTRATION

- The recommended starting dosage is 10 mg or 20 mg orally once daily based on eGFR and serum potassium thresholds. (2.1)
- Increase dosage after 4 weeks to the target dose of 20 mg once daily for CKD and T2DM based on eGFR and serum potassium thresholds. (2.3)
- Increase dosage after 4 weeks to the target dose of 20 mg or 40 mg once daily for HF with LVEF ≥ 40% based on eGFR and serum potassium thresholds. (2.3)
- Tablets may be taken with or without food (2.2)

3 DOSAGE FORMS AND STRENGTHS

Tablets: 10 mg, 20 mg, and 40 mg (3)

4 CONTRAINDICATIONS

- Concomitant use with strong CYP3A4 inhibitors. (4, 7.1)
- Patients with adrenal insufficiency. (4)
- Hypersensitivity to any component of this product. (4)

5 WARNINGS AND PRECAUTIONS

- Hyperkalemia. Patients with decreased kidney function and higher baseline potassium levels are at increased risk. Monitor serum potassium levels and adjust dose as needed. (2.1, 2.2, 2.3, 5.1)
- Worsening of Renal Function in Patients with Heart Failure. Measure eGFR and adjust dose as needed. (2.1, 2.3, 6.1)

6 ADVERSE REACTIONS

Adverse reactions occurring in ≥ 1% of patients on Kerendia and more frequently than placebo are hyperkalemia, hypotension, and hyponatremia. (6.1)

To report SUSPECTED ADVERSE REACTIONS, contact Bayer HealthCare Pharmaceuticals Inc. at 1-888-842-2937 or FDA at 1-800-FDA-1088 or www.fda.gov/medwatch.

7 DRUG INTERACTIONS

- Strong CYP3A4 Inhibitors: Use is contraindicated. (7.1)
- Grapefruit or grapefruit juice: Avoid concomitant use. (7.1)
- Moderate or weak CYP3A4 Inhibitors: Monitor serum potassium during drug initiation or dosage adjustment of either Kerendia or the moderate or weak CYP3A4 inhibitor, and adjust Kerendia dosage as appropriate (7.1)
- Strong or moderate CYP3A4 Inducers: Avoid concomitant use. (7.1)
- Sensitive CYP2C8 substrates at Kerendia 40 mg: Monitor more frequently for adverse reactions. (7.2)

8 USE IN SPECIFIC POPULATIONS

Lactation: Breastfeeding not recommended (8.2)

FULL PRESCRIBING INFORMATION

1 INDICATIONS AND USAGE

Kerendia is indicated to reduce the risk of:

- sustained estimated glomerular filtration rate (eGFR) decline, end-stage kidney disease, cardiovascular death, non-fatal myocardial infarction, and hospitalization for heart failure in adult patients with chronic kidney disease (CKD) associated with type 2 diabetes (T2DM).
- cardiovascular death, hospitalization for heart failure, and urgent heart failure visits in adult patients with heart failure with left ventricular ejection fraction (LVEF) ≥ 40%.

2 DOSAGE AND ADMINISTRATION

2.1 Prior to Initiation of Kerendia

Measure serum potassium levels and eGFR before initiation. Do not initiate treatment if serum potassium is > 5.0 mEq/L [see Warnings and Precautions (5.1)].

2.2 Recommended Starting Dosage

The recommended starting dose of Kerendia is based on eGFR and is presented in Table 1.

Table 1: Recommended Starting Dosage
eGFR (mL/min/1.73m^2) | Starting Dose
≥ 60 | 20 mg orally once daily
≥ 25 to < 60 | 10 mg orally once daily
< 25 | Initiation is not recommended

For patients who are unable to swallow whole tablets, Kerendia may be crushed and mixed with water or soft foods such as applesauce immediately prior to use and administered orally [see Clinical Pharmacology (12.3)].

2.3 Monitoring and Dosage Adjustment

CKD associated with T2DM

The target daily dose of Kerendia is 20 mg orally.

Measure serum potassium 4 weeks after initiating treatment and adjust dose (see Table 2); if serum potassium levels are > 4.8 to 5.0 mEq/L, initiation of Kerendia treatment may be considered with additional serum potassium monitoring within the first 4 weeks based on clinical judgment and serum potassium levels [see Warnings and Precautions (5.1)]. Measure serum potassium 4 weeks after a dose adjustment and periodically throughout treatment, and adjust the dose as needed (see Table 2) [see Warnings and Precautions (5.1) and Drug Interactions (7.1)].

Table 2: Dose Adjustment Based on Current Serum Potassium Concentration and Current Dose (CKD associated with T2DM)
 |  | Current Kerendia Dose
 |  | 10 mg once daily | 20 mg once daily
Current Serum Potassium (mEq/L) | ≤ 4.8 | Increase the dose to 20 mg once daily. [If eGFR has decreased by more than 30% compared to previous measurement, maintain 10 mg dose.] | Maintain 20 mg once daily.
Current Serum Potassium (mEq/L) | > 4.8 – 5.5 | Maintain 10 mg once daily. | Maintain 20 mg once daily.
Current Serum Potassium (mEq/L) | > 5.5 | Withhold Kerendia. Consider restarting at 10 mg once daily when serum potassium ≤ 5.0 mEq/L. | Withhold Kerendia. Restart at 10 mg once daily when serum potassium ≤ 5.0 mEq/L.

Heart Failure with LVEF ≥ 40%

The target daily dose of Kerendia for heart failure (LVEF ≥ 40%) is dependent on renal function (eGFR) at initiation of Kerendia treatment (see Table 3).

- The target daily dose is 40 mg orally once daily if eGFR at initiation is ≥ 60 mL/min/1.73m^2.
- The target daily dose is 20 mg orally once daily if eGFR at initiation is ≥ 25 to < 60 mL/min/1.73m^2.

Measure serum potassium and eGFR 4 weeks after initiating treatment and adjust dose (see Table 3). Measure serum potassium and eGFR 4 weeks after a dose adjustment and monitor periodically throughout treatment, and adjust the dose as needed (see Table 3) [see Warnings and Precautions (5.1 & 5.2) and Drug Interactions (7.1)].

Table 3: Dose Adjustment Based on Current Serum Potassium Concentration, eGFR, and Current Dose (Heart Failure (LVEF ≥ 40%))
 |  | Current Kerendia Dose
 |  | 10 mg once daily | 20 mg once daily | 40 mg once daily
Current Serum Potassium (mEq/L) | < 5.0 | Increase the dose to 20 mg once daily [If eGFR has decreased by more than 30% compared to previous measurement, maintain current dose.] | Maintain 20 mg once daily if eGFR < 60 mL/min/1.73 m^2 at initiation. Otherwise increase the dose to 40 mg once daily | Maintain 40 mg once daily.
Current Serum Potassium (mEq/L) | ≥ 5.0 to < 5.5 | Maintain current dose.
Current Serum Potassium (mEq/L) | ≥ 5.5 to < 6.0 | Withhold Kerendia. Restart at 10 mg once daily when serum potassium < 5.5 mEq/L. | Decrease to 10 mg once daily. | Decrease to 20 mg once daily.
Current Serum Potassium (mEq/L) | ≥ 6.0 | Withhold Kerendia. Restart at 10 mg once daily when serum potassium < 5.5 mEq/L. [If repeated serum potassium measurements are ≥5.5 mEq/L, restart Kerendia at 10 mg once daily when serum potassium < 5.0 mEq/L.]

2.4 Missed Doses

Direct a patient to take a missed dose as soon as possible after it is noticed, but only on the same day. If this is not possible, the patient should skip the dose and continue with the next dose as prescribed.

3 DOSAGE FORMS AND STRENGTHS

Kerendia is available as film-coated, oblong tablets in three strengths.

- 10 mg: pink, with "FI" on one side, "10" on the other side.
- 20 mg: yellow, with "FI" on one side, "20" on the other side.
- 40 mg: gray-orange, with "FI" on one side, "40" on the other side.

4 CONTRAINDICATIONS

Kerendia is contraindicated in patients:

- Who are hypersensitive to any component of this product [see Adverse Reactions (6.2)].
- Who are receiving concomitant treatment with strong CYP3A4 inhibitors [see Drug Interactions (7.1)].
- With adrenal insufficiency.

5 WARNINGS AND PRECAUTIONS

5.1 Hyperkalemia

Kerendia can cause hyperkalemia [see Adverse Reactions (6.1)].

The risk for developing hyperkalemia increases with decreasing kidney function and is greater in patients with higher baseline potassium levels or other risk factors for hyperkalemia. Measure serum potassium and eGFR in all patients before initiation of treatment with Kerendia and dose accordingly [see Dosage and Administration (2.1)]. Do not initiate Kerendia if serum potassium is > 5.0 mEq/L.

Measure serum potassium periodically during treatment with Kerendia and adjust dose accordingly [see Dosage and Administration (2.3)]. More frequent monitoring may be necessary for patients at risk for hyperkalemia, including those on concomitant medications that impair potassium excretion or increase serum potassium [see Drug Interactions (7.1, 7.2)].

5.2 Worsening of Renal Function in Patients with Heart Failure

Kerendia can cause worsening of renal function in patients with heart failure. Rarely, severe events associated with worsening renal function, including events requiring hospitalization, have been observed [see Adverse Reactions (6.1)].

Measure eGFR in all patients before initiation of treatment or with dose titration of Kerendia and dose accordingly [see Dosage and Administration (2.1, 2.3)]. Initiation of Kerendia in patients with heart failure and an eGFR <25 mL/min/1.73m^2 is not recommended.

Measure eGFR periodically during maintenance treatment with Kerendia in patients with heart failure. Consider delaying up-titration or interrupting treatment with Kerendia in patients who develop clinically significant worsening of renal function.

6 ADVERSE REACTIONS

The following serious adverse reactions are discussed elsewhere in the labeling:

- Hyperkalemia [see Warnings and Precautions (5.1)]

6.1 Clinical Trials Experience

Because clinical trials are conducted under widely varying conditions, adverse reaction rates observed in the clinical trials of a drug cannot be directly compared to rates in the clinical trials of another drug and may not reflect the rates observed in practice.

CKD associated with T2DM

The safety of Kerendia in patients with CKD associated with T2DM was evaluated in 2 randomized, double-blind, placebo-controlled, multicenter pivotal phase 3 studies, FIDELIO-DKD and FIGARO-DKD, in which a total of 6510 patients were treated with 10 or 20 mg once daily over a mean duration of 2.2 and 2.9 years, respectively.

Overall, serious adverse events occurred in 32% of patients receiving Kerendia and in 34% of patients receiving placebo in the FIDELIO-DKD study; the findings were similar in the FIGARO-DKD study. Permanent discontinuations due to adverse events also occurred in a similar proportion of patients in the two studies (6-7% of patients receiving Kerendia and in 5-6% of patients receiving placebo).

The most frequently reported (≥ 10%) adverse reaction was hyperkalemia [see Warnings and Precautions (5.1)]. Hospitalization due to hyperkalemia for the Kerendia group was 0.9% vs 0.2% in the placebo group across both studies. Hyperkalemia led to permanent discontinuation of treatment in 1.7% receiving Kerendia versus 0.6% of patients receiving placebo across both studies.

Table 4 shows adverse reactions that occurred more commonly on Kerendia than on placebo, and in at least 1% of patients treated with Kerendia.

Table 4: Adverse reactions reported in ≥ 1% of patients on Kerendia and more frequently than placebo (Pooled data from FIDELIO-DKD and FIGARO-DKD)
Adverse reactions | Kerendia N = 6510 n (%) | Placebo N = 6489 n (%)
Hyperkalemia | 912 (14.0) | 448 (6.9)
Hypotension | 302 (4.6) | 194 (3.0)
Hyponatremia | 82 (1.3) | 47 (0.7)

Heart Failure with LVEF ≥ 40%

The safety of Kerendia in patients with heart failure (LVEF ≥40%) was evaluated in the randomized, double-blind, placebo-controlled, multicenter pivotal phase 3 study, FINEARTS-HF, in which a total of 2,993 patients were treated with 10 mg, 20 mg, or 40 mg once daily of Kerendia with a mean duration of treatment of 2.3 years.

The overall safety profile of Kerendia in the FINEARTS-HF study was largely consistent with the adverse reactions reported in patients with CKD and T2DM (Table 4). However, adverse reactions related to worsening renal function were reported more frequently in the Kerendia group (18%) compared with placebo (12%) in FINEARTS-HF. The most frequently reported adverse reactions included renal impairment (7% vs. 4%), eGFR decreased (5% vs. 4%), acute kidney injury (4% vs. 2%) and renal failure (3% vs. 2%). The majority of events were reported to be mild to moderate. These events led to dose modifications in 9% of patients receiving Kerendia versus 4% of patients receiving placebo. Hospitalization due to events related to worsening of renal function for the Kerendia group was 2.0% versus 1.3% in the placebo group.

Laboratory Test

Initiation of Kerendia may cause an initial small increase in blood creatinine levels (mean change <0.1 mg/dL) and a small decrease in eGFR (mean change 2-3 ml/min) that occurs within the first 4 weeks of starting therapy and then stabilizes. These changes were reversible after treatment discontinuation. Initiation of Kerendia may also cause a small increase in serum uric acid. This increase appears to attenuate over time.

6.2 Postmarketing Experience

The following additional adverse reactions have been reported in postmarketing experience with finerenone. Because these reactions are reported voluntarily from a population of uncertain size, it is not always possible to estimate their frequency reliably or to establish a causal relationship to drug exposure:

Hypersensitivity: Angioedema, Rash and Urticaria

7 DRUG INTERACTIONS

7.1 Effect of Other Drugs on Kerendia

Strong CYP3A4 Inhibitors

Kerendia is a CYP3A4 substrate. Concomitant use with a strong CYP3A4 inhibitor increases finerenone exposure [see Clinical Pharmacology (12.3)], which may increase the risk of Kerendia adverse reactions. Concomitant use of Kerendia with strong CYP3A4 inhibitors is contraindicated [see Contraindications (4)]. Avoid concomitant intake of grapefruit or grapefruit juice.

Moderate and Weak CYP3A4 Inhibitors

Kerendia is a CYP3A4 substrate. Concomitant use with a moderate or weak CYP3A4 inhibitor increases finerenone exposure [see Clinical Pharmacology (12.3)], which may increase the risk of Kerendia adverse reactions. Monitor serum potassium during drug initiation or dosage adjustment of either Kerendia or the moderate or weak CYP3A4 inhibitor, and adjust Kerendia dosage as appropriate [see Dosing and Administration (2.3) and Drug Interaction (7.2)].

Strong and Moderate CYP3A4 Inducers

Kerendia is a CYP3A4 substrate. Concomitant use of Kerendia with a strong or moderate CYP3A4 inducer decreases finerenone exposure [see Clinical Pharmacology (12.3)], which may reduce the efficacy of Kerendia. Avoid concomitant use of Kerendia with strong or moderate CYP3A4 inducers.

7.2 Effect of Kerendia on Other Drugs

CYP2C8 Substrates

Kerendia is a weak CYP2C8 inhibitor at 40 mg. Kerendia increases exposure of CYP2C8 substrates at 40 mg dose [see Clinical Pharmacology (12.3)], which may increase the risk of adverse reactions related to these substrates. Monitor patients more frequently for adverse reactions caused by sensitive CYP2C8 substrates if Kerendia 40 mg is co-administered with such substrates since minimal concentration changes may lead to serious adverse reactions.

7.3 Drugs That Affect Serum Potassium

More frequent serum potassium monitoring is warranted in patients receiving concomitant therapy with drugs or supplements that increase serum potassium. [see Dosage and Administration (2.3) and Warnings and Precautions (5.1)].

8 USE IN SPECIFIC POPULATIONS

8.1 Pregnancy

Risk Summary

There are no available data on Kerendia use in pregnancy to evaluate for a drug-associated risk of major birth defects, miscarriage, or adverse maternal or fetal outcomes. Animal studies have shown developmental toxicity at exposures about 2 times those expected in humans (see Data). The clinical significance of these findings is unclear.

The estimated background risk of major birth defects and miscarriage for the indicated population is unknown. All pregnancies have a background risk of birth defect, loss or other adverse outcomes. In the U.S. general population, the estimated background risk of major birth defects and miscarriage in clinically recognized pregnancies is 2 to 4% and 15 to 20%, respectively.

Data

Animal Data

In the embryo-fetal toxicity study in rats, finerenone resulted in reduced placental weights and signs of fetal toxicity, including reduced fetal weights and retarded ossification at the maternal toxic dose of 10 mg/kg/day corresponding to an AUCunbound of at least 7 times that in humans. At 30 mg/kg/day, the incidence of visceral and skeletal variations was increased (slight edema, shortened umbilical cord, slightly enlarged fontanelle) and one fetus showed complex malformations including a rare malformation (double aortic arch) at an AUCunbound of about 10 times that in humans at the 40 mg dose and about 25 times that in humans at the 20 mg dose. The doses free of any findings (low dose in rats, high dose in rabbits) provide safety margins of 4 to 5 times for the AUCunbound expected in humans.

When rats were exposed during pregnancy and lactation in the pre- and postnatal developmental toxicity study, increased pup mortality and other adverse effects (lower pup weight, delayed pinna unfolding) were observed at about 2 or 4 times the AUCunbound expected in humans at the dose of 40 mg and 20 mg, respectively. In addition, the offspring showed slightly increased locomotor activity, but no other neurobehavioral changes starting at about 2 or 4 times the AUCunbound expected in humans at the dose of 40 mg and 20 mg, respectively. The dose free of findings provides a safety margin of about 2 times for the AUCunbound expected in humans for the 20 mg dose and is in the therapeutic range for the 40 mg dose.

8.2 Lactation

Risk Summary

There are no data on the presence of finerenone or its metabolite in human milk, the effects on the breastfed infant or the effects of the drug on milk production. In a pre- and postnatal developmental toxicity study in rats, increased pup mortality and lower pup weight were observed at about 2 times the AUCunbound expected in humans. These findings suggest that finerenone is present in rat milk [see Use in Specific Populations (8.1) and Data]. When a drug is present in animal milk, it is likely that the drug will be present in human milk. Because of the potential risk to breastfed infants from exposure to Kerendia, avoid breastfeeding during treatment and for 1 day after treatment.

8.4 Pediatric Use

The safety and efficacy of Kerendia have not been established in patients below 18 years of age.

8.5 Geriatric Use

Of the 6510 patients who received Kerendia in the FIDELIO-DKD and FIGARO-DKD studies, 55% of patients were 65 years and older, and 14% were 75 years and older. Of the 2993 patients who received Kerendia in the FINEARTS study, 79% of patients were 65 years and older, and 43% were 75 years and older. No overall differences in safety or efficacy were observed between these patients and younger patients. No dose adjustment is required.

8.6 Hepatic Impairment

Avoid use of Kerendia in patients with severe hepatic impairment (Child Pugh C).

No dosage adjustment is recommended in patients with mild or moderate hepatic impairment (Child Pugh A or B).

Consider additional serum potassium monitoring in patients with moderate hepatic impairment (Child Pugh B) [see Dosing and Administration (2.3) and Clinical Pharmacology (12.3)].

10 OVERDOSAGE

In the event of suspected overdose, immediately interrupt Kerendia treatment. The most likely manifestation of overdose is hyperkalemia. If hyperkalemia develops, standard treatment should be initiated.

Finerenone is unlikely to be efficiently removed by hemodialysis given its fraction bound to plasma proteins of about 90%.

11 DESCRIPTION

Kerendia contains finerenone, a nonsteroidal mineralocorticoid receptor antagonist. Finerenone's chemical name is (4S)-4-(4-cyano-2- methoxyphenyl)-5-ethoxy-2,8-dimethyl-1,4-dihydro-1,6-naphthyridine-3-carboxamide. The molecular formula is C21H22N4O3 and the molecular weight is 378.43 g/mol. The structural formula is:

Finerenone is a white to yellow crystalline powder. It is practically insoluble in water; and sparingly soluble in 0.1 M HCl, ethanol, and acetone.

Each Kerendia tablet contains 10 mg, 20 mg, or 40 mg of finerenone. The inactive ingredients of Kerendia are lactose monohydrate, cellulose microcrystalline, croscarmellose sodium, hypromellose, magnesium stearate, and sodium lauryl sulfate. The film coating contains hypromellose, titanium dioxide and talc, in addition to ferric oxide red (10 mg and 40 mg strength tablets) or ferric oxide yellow (20 mg and 40 mg strength tablets).

12 CLINICAL PHARMACOLOGY

12.1 Mechanism of Action

Finerenone is a nonsteroidal, selective antagonist of the mineralocorticoid receptor (MR), which is activated by aldosterone and cortisol and regulates gene transcription. Finerenone blocks MR mediated sodium reabsorption and MR overactivation in both epithelial (e.g., kidney) and nonepithelial (e.g., heart, and blood vessels) tissues. MR overactivation is thought to contribute to fibrosis and inflammation. Finerenone has a high potency and selectivity for the MR and has no relevant affinity for androgen, progesterone, estrogen, and glucocorticoid receptors.

12.2 Pharmacodynamics

In FIDELIO-DKD and FIGARO-DKD, randomized, double-blind, placebo-controlled, multicenter studies in adult patients with chronic kidney disease associated with type 2 diabetes, the placebo-corrected relative reduction in urinary albumin-to-creatinine ratio (UACR) in patients randomized to finerenone was 31% (95% CI 29-34%), and 32% (95% CI 30-35%) respectively at Month 4 and remained stable for the duration of the trial.

In ARTS DN, a randomized, double-blind, placebo-controlled, multicenter phase IIb dose finding study in adults with CKD and T2DM, the placebo-corrected relative reduction in UACR at Day 90 was 25% and 38% in patients treated with finerenone 10 mg and 20 mg once daily, respectively. In patients treated with Kerendia, the mean systolic blood pressure decreased by 3 mmHg and the mean diastolic blood pressure decreased by 1-2 mmHg at month 1, remaining stable thereafter.

Cardiac Electrophysiology

At a dose 2 times the maximum approved recommended dose, finerenone does not prolong the QT interval to any clinically relevant extent.

12.3 Pharmacokinetics

Finerenone exposure increased proportionally over a dose range of 1.25 to 80 mg (0.06 to 4 times the maximum approved recommended dosage). Steady state of finerenone was achieved after 2 days of dosing. The estimated steady-state geometric mean Cmax,md was 166 µg/L and steady-state geometric mean AUCτ,md was 718 µg.h/L following administration of finerenone 20 mg to patients.

Absorption

Finerenone is completely absorbed after oral administration but undergoes metabolism resulting in absolute bioavailability of 44%. Finerenone Cmax was achieved between 0.5 and 1.25 hours after dosing.

Effect of Food

There was no clinically significant effect on finerenone AUC following administration with high fat, high calorie food.

Distribution

The volume of distribution at steady-state (Vss) of finerenone is 52.6 L. Plasma protein binding of finerenone is 92%, primarily to serum albumin, in vitro.

Elimination

The terminal half-life of finerenone is about 2 to 3 hours, and the systemic blood clearance is about 25 L/h.

Metabolism

Finerenone is primarily metabolized by CYP3A4 (90%) and to a lesser extent by CYP2C8 (10%) to inactive metabolites.

Excretion

About 80% of the administered dose is excreted in urine (<1% as unchanged) and approximately 20% in feces (< 0.2% as unchanged).

Specific Populations

There are no clinically significant effects of age (18 to 86 years), sex, race/ethnicity (White, Asian, Black, and Hispanic), or weight (54 to 126 kg) on the pharmacokinetics of finerenone.

Renal Impairment

There were no clinically relevant differences in finerenone AUC or Cmax values in patients with eGFR 15 to < 90 mL/min/1.73m^2 compared to eGFR ≥ 90 mL/min/1.73 m^2. For dosing recommendations based on eGFR and serum potassium levels see Dosage and Administration (2).

Hepatic Impairment

There was no clinically significant effect on finerenone exposure in cirrhotic patients with mild hepatic impairment (Child Pugh A).

Finerenone mean AUC was increased by 38% and Cmax was unchanged in cirrhotic patients with moderate hepatic impairment (Child Pugh B) compared to healthy control subjects.

The effect of severe hepatic impairment (Child Pugh C) on finerenone exposure was not studied.

Drug Interaction Studies

Clinical Studies and Model-Informed Approaches

Strong CYP3A Inhibitors: Concomitant use of itraconazole (strong CYP3A4 inhibitor) was predicted to increase finerenone AUC by >400%.

Moderate CYP3A Inhibitors: Concomitant use of erythromycin (moderate CYP3A4 inhibitor) increased finerenone mean AUC and Cmax by 248% and 88%, respectively. Concomitant use of verapamil (moderate CYP3A4 inhibitor) increased finerenone mean AUC and Cmax by 170% and 122%, respectively.

Weak CYP3A Inhibitors: Concomitant use of amiodarone (weak CYP3A4 inhibitor) increased finerenone AUC by 21%.

Strong or Moderate CYP3A Inducers: Concomitant use of efavirenz (moderate CYP3A4 inducer) and rifampicin (strong CYP3A4 inducer) was predicted to decrease finerenone AUC by 80% and 90%, respectively.

CYP3A4 Substrates: Concomitant use of multiple finerenone 40 mg doses once daily with midazolam (sensitive CYP3A4 substrate) increased the mean AUC by 31% with no effect on Cmax. There were no clinically significant differences in the pharmacokinetics of midazolam when used concomitantly with multiple finerenone 20 mg doses once daily.

CYP2C8 Substrates: Concomitant use of multiple finerenone 40 mg doses once daily with repaglinide (sensitive CYP2C8 substrate) increased the mean AUC and Cmax of repaglinide by 59% and 30%, respectively. There were no clinically significant differences in the pharmacokinetics of repaglinide when used concomitantly with multiple finerenone 20 mg doses once daily.

Other Drugs: No clinically significant differences in the pharmacokinetics of the following drugs were observed or predicted when used concomitantly with finerenone: S-warfarin (CYP2C9 substrate), digoxin (P-gp substrate), and rosuvastatin (BCRP and OATP substrate). There was no clinically significant difference in finerenone pharmacokinetics when used concomitantly with gemfibrozil (strong CYP2C8 inhibitor).

13 NONCLINICAL TOXICOLOGY

13.1 Carcinogenesis, Mutagenesis, Impairment of Fertility

Finerenone was non-genotoxic in an in vitro bacterial reverse mutation (Ames) assay, the in vitro chromosomal aberration assay in cultured Chinese hamster V79 cells, or the in vivo micronucleus assay in mice.

In 2-year carcinogenicity studies, finerenone did not show a statistically significant increase in tumor response in Wistar rats or in CD1 mice. In male mice, Leydig cell adenoma was numerically increased at a dose representing 10 times the AUCunbound in humans and is not considered clinically relevant. Finerenone did not impair fertility in male rats but impaired fertility in female rats at 9 times AUC to the maximum human exposure.

14 CLINICAL STUDIES

14.1 CKD associated with T2DM

FIDELIO-DKD (NCT: 02540993) and FIGARO-DKD (NCT: 02545049) studies were randomized, double-blind, placebo-controlled, multicenter studies in adult patients with chronic kidney disease (CKD) associated with type 2 diabetes (T2DM). In FIDELIO-DKD, patients needed to either have an UACR of 30 to < 300 mg/g, eGFR 25 to < 60 mL/min/1.73 m^2 and diabetic retinopathy, or an UACR of ≥ 300 mg/g and an eGFR of 25 to < 75 mL/min/1.73 m^2 to qualify for enrollment. In FIGARO-DKD, patients needed to have an UACR of 30 mg/g to < 300 mg/g and an eGFR of 25 to 90 mL/min/1.73m^2, or an UACR ≥ 300 mg/g and an eGFR ≥ 60 mL/min/1.73m^2.

Both trials excluded patients with known significant non-diabetic kidney disease. All patients were to have a serum potassium ≤ 4.8 mEq/L at screening and be receiving standard of care background therapy, including a maximum tolerated labeled dose of an angiotensin-converting enzyme inhibitor (ACEi) or angiotensin receptor blocker (ARB). Patients with a clinical diagnosis of chronic heart failure with reduced ejection fraction and persistent symptoms (New York Heart Association class II to IV) were excluded. The starting dose of Kerendia was based on screening eGFR (10 mg once daily in patients with an eGFR of 25 to < 60 mL/min/1.73 m^2 and 20 mg once daily in patients with an eGFR ≥ 60 mL/min/1.73 m^2). The dose of Kerendia could be titrated during the study, with a target dose of 20 mg daily.

The primary objective of the FIDELIO-DKD study was to determine whether Kerendia reduced the incidence of a sustained decline in eGFR of ≥ 40%, kidney failure (defined as chronic dialysis, kidney transplantation, or a sustained decrease in eGFR to < 15 mL/min/1.73 m^2), or renal death. The secondary outcome was a composite of time to first occurrence of CV death, non-fatal MI, non-fatal stroke or hospitalization for heart failure. The primary objective of the FIGARO-DKD study was to determine whether Kerendia reduced the time to first occurrence of CV death, non-fatal MI, non-fatal stroke or hospitalization for heart failure. The secondary outcome was a composite of time to kidney failure, a sustained decline in eGFR of 40% or more compared to baseline over at least 4 weeks, or renal death.

In FIDELIO-DKD, a total of 5674 patients were randomized to receive Kerendia (N=2833) or placebo (N=2841) and were followed for a median of 2.6 years. The mean age of the study population was 66 years, and 70% of patients were male. This global trial population was 63% White, 25% Asian, and 5% Black. At baseline, the mean eGFR was 44 mL/min/1.73m^2, with 55% of patients having an eGFR < 45 mL/min/1.73m^2. Median urine albumin-to-creatinine ratio (UACR) was 852 mg/g, mean glycated hemoglobin A1c (HbA1c) was 7.7%, and the mean blood pressure was 138/76 mmHg. Approximately 46% of patients had a history of atherosclerotic cardiovascular disease and 8% had a history of heart failure. At baseline, 99.8% of patients were treated with an ACEi or ARB. Approximately 97% were on an antidiabetic agent (insulin [64.1%], biguanides [44%], glucagon-like peptide-1 [GLP-1] receptor agonists [7%], sodium-glucose cotransporter 2 [SGLT2] inhibitors [5%]), 74% were on a statin, and 57% were on an antiplatelet agent.

In FIGARO-DKD, a total of 7352 patients were randomized to receive Kerendia (N=3686) or placebo (N=3666) and were followed for 3.4 years. As compared to FIDELIO-DKD, baseline eGFR was higher in FIGARO-DKD (mean eGFR 68, with 62% of patients having an eGFR ≥ 60 mL/min/1.73 m^2) and median UACR was lower (308 mg/g). Otherwise, baseline patient characteristics and background therapies were similar in the two trials.

In FIDELIO-DKD, Kerendia reduced the incidence of the primary composite endpoint of a sustained decline in eGFR of ≥ 40%, kidney failure, or renal death (HR 0.82, 95% CI 0.73-0.93, p=0.001) as shown in Table 5 and Figure 1. The treatment effect reflected a reduction in a sustained decline in eGFR of ≥ 40% and progression to kidney failure. There were few renal deaths during the trial. Kerendia also reduced the incidence of the secondary composite endpoint of cardiovascular (CV) death, non-fatal myocardial infarction (MI), non-fatal stroke or hospitalization for heart failure (HR 0.86, 95% CI 0.75-0.99, p=0.034) as shown in Table 5 and Figure 3. The treatment effect reflected a reduction in CV death, non-fatal MI, and hospitalization for heart failure. The treatment effect on the primary and secondary composite endpoints was generally consistent across subgroups.

In FIGARO-DKD, Kerendia reduced the incidence of the primary composite endpoint of CV death, non-fatal MI, non-fatal stroke or hospitalization for heart failure (HR 0.87, 95% CI 0.76-0.98, p = 0.026) as shown in Table 5 and Figure 4. The treatment effect was mainly driven by an effect on hospitalization for heart failure, though CV death also contributed to the treatment effect. The treatment effect on the primary composite endpoint was generally consistent across subgroups, including patients with and without pre-existing cardiovascular disease. The findings for the renal composite endpoint are shown in Table 5 and Figure 2.

Table 5: Analysis of the Primary and Secondary Time-to-Event Endpoints (and their Individual Components) in Phase 3 Studies FIDELIO-DKD and FIGARO-DKD
 | FIDELIO-DKD |  |  |  | FIGARO-DKD
 | Kerendia N=2833 | Placebo N=2841 | Treatment Effect Kerendia / Placebo |  | Kerendia N=3686 | Placebo N=3666 | Treatment Effect Kerendia / Placebo
Time-to-event Endpoints: | Event Rate (100 pt-yr) | Event Rate (100 pt-yr) | Hazard Ratio (95% CI) | p-value | Event Rate (100 pt-yr) | Event Rate (100 pt-yr) | Hazard Ratio (95% CI) | p-value
Composite of kidney failure, sustained eGFR decline ≥40% or renal death | 7.6 | 9.1 | 0.82 [0.73; 0.93] | 0.001 | 3.2 | 3.6 | 0.87 [0.76; 1.01] | -
Kidney failure | 3.0 | 3.4 | 0.87 [0.72; 1.05] | - | 0.4 | 0.5 | 0.72 [0.49;1.05] | -
Sustained eGFR decline ≥40% | 7.2 | 8.7 | 0.81 [0.72; 0.92] | - | 3.1 | 3.5 | 0.87 [0.75;>1.00] | -
Renal death | - | - | - | - | - | - | - | -
Composite of CV death, non-fatal MI, non-fatal stroke or hospitalization for heart failure | 5.1 | 5.9 | 0.86 [0.75; 0.99] | 0.034 | 3.9 | 4.5 | 0.87 [0.76; 0.98] | 0.026
CV death | 1.7 | 2.0 | 0.86 [0.68;1.08] | - | 1.6 | 1.8 | 0.90 [0.73; 1.08] | -
Non-fatal MI | 0.9 | 1.2 | 0.80 [0.58;1.09] | - | 0.9 | 0.8 | 0.99 [0.76; 1.32] | -
Non-fatal stroke | 1.2 | 1.2 | 1.03 [0.76;1.38] | - | 0.9 | 0.9 | 0.97 [0.74; 1.26] | -
Hospitalization for heart failure | 1.9 | 2.2 | 0.86 [0.68;1.08] | - | 1.0 | 1.4 | 0.71 [0.56; 0.90] | -
p-value: two-sided p-value from stratified logrank test
CI = confidence interval, CV = cardiovascular, eGFR = estimated glomerular filtration rate, MI = myocardial infarction, N = number of subjects, n = number of subjects with event, pt-yr = patient year.
NOTE: Time to first event was analyzed in a Cox proportional hazards model. For patients with multiple events, only the first event contributed to the composite endpoint. Sums of the numbers of first events for the single components do not add up to the numbers of events in the composite endpoint.

Figure 1: Time to first occurrence of kidney failure, sustained decline in eGFR ≥ 40% from baseline, or renal death in the FIDELIO-DKD study

Figure 2: Time to first occurrence of kidney failure, sustained decline in eGFR ≥ 40% from baseline, or renal death in the FIGARO-DKD study

Figure 3: Time to first occurrence of CV death, non-fatal myocardial infarction, non-fatal stroke or hospitalization for heart failure in the FIDELIO-DKD study

Figure 4: Time to first occurrence of CV death, non-fatal myocardial infarction, non-fatal stroke or hospitalization for heart failure in the FIGARO-DKD study

14.2 Heart Failure (LVEF ≥40%)

FINEARTS-HF (NCT: 04435626) was a randomized, double-blind, placebo-controlled, multicenter study in adult patients with heart failure (New York Heart Association [NYHA] class II–IV) with documented left ventricular ejection fraction (LVEF) ≥40%. Patients were required to have an eGFR ≥25 mL/min/1.73m^2 and serum potassium ≤5.0 mEq/L at screening and randomization and were receiving background heart failure medical treatment, including diuretics. The primary endpoint was the composite of cardiovascular (CV) death and total (first and recurrent) heart failure events comprised of hospitalization for heart failure and urgent heart failure visits.

In FINEARTS-HF, 6001 patients were analyzed; 3003 were randomized to Kerendia and 2998 were randomized to placebo and were followed for a median of 2.7 years. The study included 3247 (54%) patients with a heart failure event in the past 3 months, including 1219 (20%) patients randomized during the hospitalization or within 7 days from the heart failure event. Patients with eGFR ≥ 25 to <60 mL/min/1.73m^2 initiated Kerendia 10 mg and patients with eGFR ≥60 mL/min/1.73m^2 initiated Kerendia 20 mg, and both groups were titrated up to a target dose of Kerendia 20 mg and 40 mg, respectively. At month 6, approximately 65% of the patients reached their target dose. The trial population was 79% White, 17% Asian, and 1.5% Black. The mean age at enrollment was 72 years and 46% of patients were female. At baseline, the mean LVEF was 53%, with 64% of patients having an LVEF ≥50%, and 69% and 30% of patients were NYHA class II and III, respectively. Mean blood pressure was 129/75 mmHg and mean body mass index (BMI) was 30 kg/m^2. The median NT-proBNP was 1041 pg/mL, the mean eGFR was 62 mL/min/1.73m^2 with 48% of patients having an eGFR <60 mL/min/1.73m^2. Atrial fibrillation was present on screening/baseline ECG for 38% of patients and 41% had diabetes mellitus. The majority of patients were on loop diuretics (87%), an angiotensin-converting enzyme inhibitor (ACEi) or angiotensin receptor blocker (ARB) (79%), or an angiotensin receptor neprilysin inhibitor (ARNI) (9%), and 14% were on sodium-glucose cotransporter 2 (SGLT2) inhibitors.

Kerendia reduced the risk of the primary composite endpoint compared to placebo (Relative Risk [RR] 0.84, 95% CI 0.74-0.95, p=0.007). See Table 6 and Figure 5 below. The Kerendia and placebo event curves separated early and continued to diverge over the study period, see Figure 5 below. Kerendia reduced the risk of the secondary endpoint of total heart failure events (hospitalization for HF or urgent HF visit) compared to placebo (RR 0.82, 95% CI 0.71-0.94, p=0.006). The treatment effect for the primary endpoint was consistent across all pre-specified subgroups, including sex, LVEF, NYHA class, eGFR, time since latest heart failure event, SGLT2 inhibitor therapy, and diabetes mellitus status.

Table 6: Analysis of the Primary Endpoint (and its Individual Components) and Secondary Endpoint in Phase 3 Study FINEARTS-HF
 | FINEARTS-HF
 | Kerendia 10 or 20 or 40 mg OD N=3003 |  | Placebo N=2998 |  | Treatment Effect Kerendia vs Placebo
Primary Efficacy Outcome and Components: | Value | Event Rate (100 pt–yr) | Value | Event Rate (100 pt–yr) | Ratio or difference (95% CI) | p-value
Primary composite of CV death and total HF events – E (n; %) | 1083 (624; 20.8%) | 14.9 | 1283 (719; 24.0%) | 17.7 | RR 0.84 (0.74, 0.95) | 0.007
Total HF events – E (n; %) [Total HF events (hospitalization for HF or urgent HF visit) was a prespecified secondary endpoint.] | 842 (479; 16.0%) | 11.6 | 1024 (573; 19.1%) | 14.1 | RR 0.82 (0.71, 0.94) | 0.006
CV death – n (%) | 242 (8.1%) | 3.3 | 260 (8.7%) | 3.6 | HR 0.93 (0.78, 1.11) | -
E = total number of events; n = number of patients with an event ; RR = rate ratio; HR = hazard ratio; HF = Heart Failure; CV = Cardiovascular.

Figure 5: Mean cumulative functions for primary composite endpoint of CV death and total HF events in Phase 3 study FINEARTS-HF

16 HOW SUPPLIED/STORAGE AND HANDLING

16.1 How Supplied

Kerendia is available as a film-coated tablet in three strengths. The 10 mg is a pink oblong tablet with "FI" on one side of tablet and "10" on the other side of tablet. The 20 mg tablet is a yellow oblong tablet with "FI" on one side of tablet and "20" on the other side of tablet. The 40 mg tablet is a gray-orange oblong tablet with "FI" on one side of tablet and "40" on the other side of tablet.

Kerendia Tablets 10 mg
Bottle of 30 tablets | NDC 50419-540-01
Bottle of 90 tablets | NDC 50419-540-02
Hospital Blister Pack of 30 tablets | NDC 50419-540-06
Kerendia Tablets 20 mg
Bottle of 30 tablets | NDC 50419-541-01
Bottle of 90 tablets | NDC 50419-541-02
Hospital Blister Pack of 30 tablets | NDC 50419-541-06
Kerendia Tablets 40 mg
Bottle of 30 tablets | NDC 50419-542-01
Bottle of 90 tablets | NDC 50419-542-02
Hospital Blister Pack of 30 tablets | NDC 50419-542-06

16.2 Storage and Handling

Store at 20°C to 25°C (68°F to 77°F); excursions are permitted from 15°C to 30°C (59°F to 86°F) [see USP Controlled Room Temperature].

17 PATIENT COUNSELING INFORMATION

Advise patients of the need for periodic monitoring of serum potassium levels. Advise patients receiving Kerendia to consult with their physician before using potassium supplements or salt substitutes containing potassium [see Warnings and Precautions (5.1)].

Advise patients to avoid strong or moderate CYP3A4 inducers and to find alternative medicinal products with no or weak potential to induce CYP3A4 [see Drug Interactions (7.1)]

Avoid concomitant intake of grapefruit or grapefruit juice as it is expected to increase the plasma concentration of finerenone [see Drug Interactions (7.1)].

Advise women that breastfeeding is not recommended at the time of treatment with KERENDIA and for 1 day after treatment [see Use in Specific Populations (8.2)].

© 2021, Bayer HealthCare Pharmaceuticals Inc., All rights reserved.

Manufactured for:

Bayer HealthCare Pharmaceuticals Inc.
Whippany, NJ 07981

Manufactured in Germany

PRINCIPAL DISPLAY PANEL- 10 mg Tablet Carton

NDC 50419-540-01
Rx only

Kerendia®
(finerenone) tablets
10 mg

30 film-coated tablets

BAYER

PRINCIPAL DISPLAY PANEL- 20 mg Tablet Carton

NDC 50419-541-01
Rx only

Kerendia®
(finerenone) tablets
20 mg

30 film-coated tablets

BAYER

PRINCIPAL DISPLAY PANEL- 40 mg Tablet Carton

NDC 50419-542-01
Rx only

Kerendia®
(finerenone) tablets
40 mg

30 film-coated tablets

BAYER